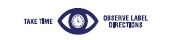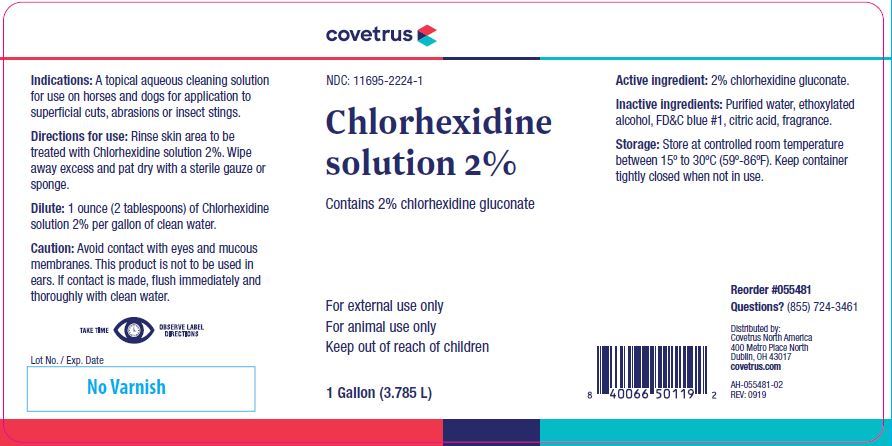 DRUG LABEL: Chlorhexidine solution
NDC: 11695-2224 | Form: SOLUTION
Manufacturer: Butler Animal Health Supply, LLC dba Covetrus North America
Category: animal | Type: OTC ANIMAL DRUG LABEL
Date: 20191111

ACTIVE INGREDIENTS: CHLORHEXIDINE GLUCONATE 99.0 g/1 L

Chlorhexidine solution 2%

STATEMENT OF IDENTITY

Contains 2% chlorhexidine gluconate

KEEP OUT OF REACH OF CHILDREN

For external use only
For animal use only
Keep out of reach of children

HOW SUPPLIED

1 Gallon (3.785 L)

Indications:

A topical aqueous cleaning solution for use on horses and dogs for application to superficial cuts, abrasions or insect stings.

Directions for use:

Rinse skin area to be treated with Chlorhexidine solution 2%. Wipe away excess and pat dry with a sterile gauze or sponge.

Dilute:

1 ounce (2 tablespoons) of Chlorhexidine solution 2% per gallon of clean water.

Caution:

Avoid contact with eyes and mucous membranes. This product is not to be used in ears. If contact is made, flush immediately and thoroughly with clean water.

Active ingredient:

2% chlorhexidine gluconate.

Inactive ingredients:

Purified water, ethoxylated alcohol, FD&C blue #1, citric acid, fragrance.

Storage:

Store at controlled room temperature between 15º to 30ºC (59º-86ºF). Keep container tightly closed when not in use.

QUESTIONS

Reorder #055481
Questions? (855) 724-3461
Distributed by:
Covetrus North America
400 Metro Place North
Dublin, OH 43017
covetrus.com

AH-055481-02
REV: 0919